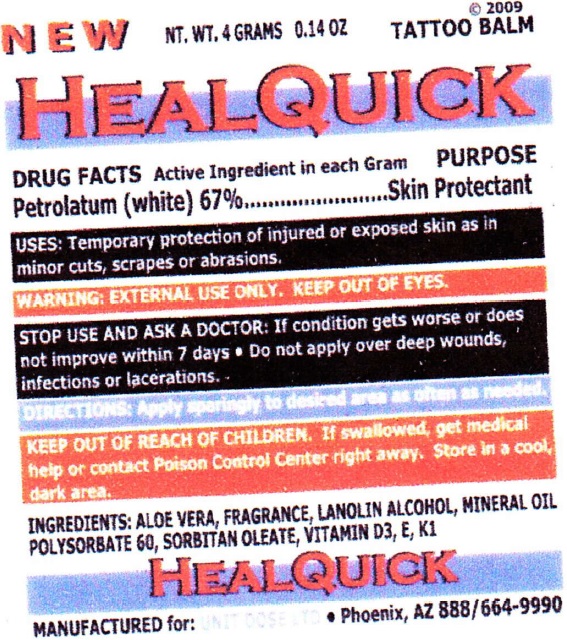 DRUG LABEL: Healquick Tattoo Balm
NDC: 67194-012 | Form: STICK
Manufacturer: Unit Dose, Ltd.
Category: otc | Type: HUMAN OTC DRUG LABEL
Date: 20231019

ACTIVE INGREDIENTS: PETROLATUM 670 mg/1 g
INACTIVE INGREDIENTS: ALOE VERA LEAF; LANOLIN ALCOHOLS; MINERAL OIL; POLYSORBATE 60; SORBITAN MONOOLEATE; CHOLECALCIFEROL; .ALPHA.-TOCOPHEROL; PHYTONADIONE

Healquick Tattoo Balm

Active Ingredient in each Gram

Petrolatum (White) 67%

PURPOSE

Skin Protectant

USES:

Temporary protection of injured or exposed skin as in minor cuts, scrapes or abrasions.

WARNINGS:

EXTERNAL USE ONLY. KEEP OUT OF EYES.

STOP USE AND ASK A DOCTOR:

If condition gets worse or does not improve within 7days. Do not apply over deep wounds, infections or lacerations.

DIRECTIONS:

Apply sparingly to desired area as often as needed

KEEP OUT OF REACH OF CHILDREN:

If swallowed, get medical help or contact a Poison Control Center right away. Store in a cool, dark area.

INGREDIENTS:

ALOE VERA, FRAGRANCE, LANOLIN ALCOHOL, MINERAL OIL, POLYSORBATE 60, SORBITAN OLEATE, VITAMIN D3, E, K1